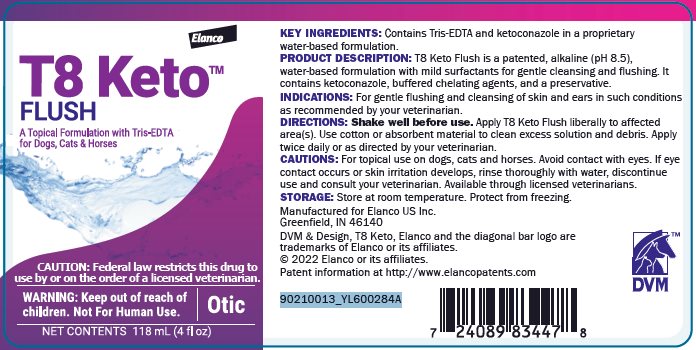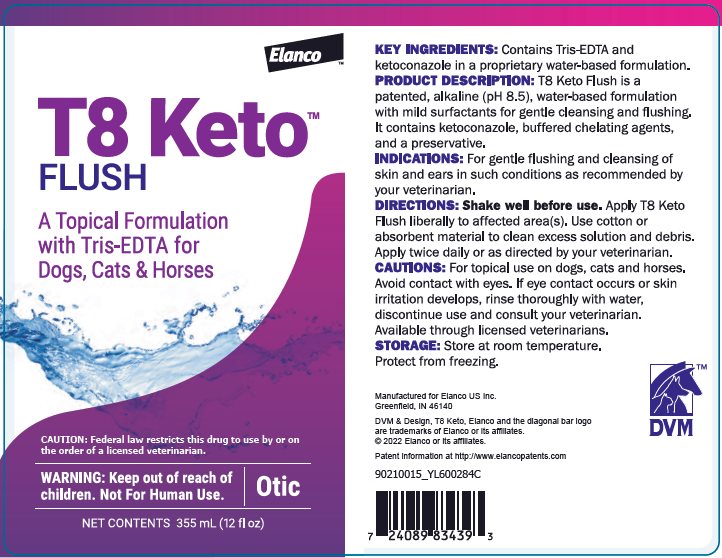 DRUG LABEL: T8 Keto Flush
NDC: 58198-0013 | Form: SOLUTION
Manufacturer: Elanco US Inc.
Category: animal | Type: PRESCRIPTION ANIMAL DRUG LABEL
Date: 20251028

ACTIVE INGREDIENTS: Ketoconazole 1 mg/1 mL

Elanco™
T8 Keto™
FLUSH

A Topical Formulation with Tris-EDTA for Dogs, Cats & Horses

CAUTION: Federal law restricts this drug to use by or on the order of a licensed veterinarian.

WARNING: Keep out of reach of children. Not For Human Use.

Otic

Net Contents: 118 mL (4 fl oz)

Net Contents: 355 mL (12 fl oz)

KEY INGREDIENTS:

Contains Tris-EDTA and ketoconazole in a proprietary water-based formulation.

PRODUCT DESCRIPTION:

T8 Keto Flush is a patented, alkaline (pH 8.5), water-based formulation with mild surfactants for gentle cleansing and flushing. It contains ketoconazole, buffered chelating agents, and a preservative.

INDICATIONS:

For gentle flushing and cleansing of skin and ears in such conditions as recommended by your veterinarian.

DIRECTIONS:

Shake well before use. Apply T8 Keto Flush liberally to affected area(s). Use cotton or absorbent material to clean excess solution and debris. Apply twice daily or as directed by your veterinarian.

CAUTIONS: For topical use on dogs, cats and horses. Avoid contact with eyes. If eye contact occurs or skin irritation develops, rinse thoroughly with water, discontinue use and consult your veterinarian. Available through licensed veterinarians.

STORAGE:

Store at room temperature. Protect from freezing.

Manufactured for Elanco US Inc.
Greenfield, IN 46140

DVM & Design, T8 Keto, Elanco and the diagonal bar logo are trademarks of Elanco or its affiliates.

© 2022 Elanco or its affiliates.

Patent information at http://www.elancopatents.com

90210013_YL600284A
90210015_YL600284C

Principal Display Panel – 118 mL Bottle Label

Elanco™

T8 KetoTM
FLUSH

A Topical Formulation with Tris-EDTA
for Dogs, Cats & Horses

CAUTION: Federal law restricts this drug to
use by or on the order of a licensed veterinarian.

WARNING: Keep out of reach of
children. Not For Human Use.

Otic

NET CONTENTS 118 mL (4 fl oz)

Principal Display Panel – 355 mL Bottle Label

Elanco™

T8 KetoTM
FLUSH

A Topical Formulation
with Tris-EDTA for
Dogs, Cats & Horses

CAUTION: Federal law restricts this drug to use by or on
the order of a licensed veterinarian.

WARNING: Keep out of reach of
children. Not For Human Use.

Otic

NET CONTENTS 355 mL (12 fl oz)